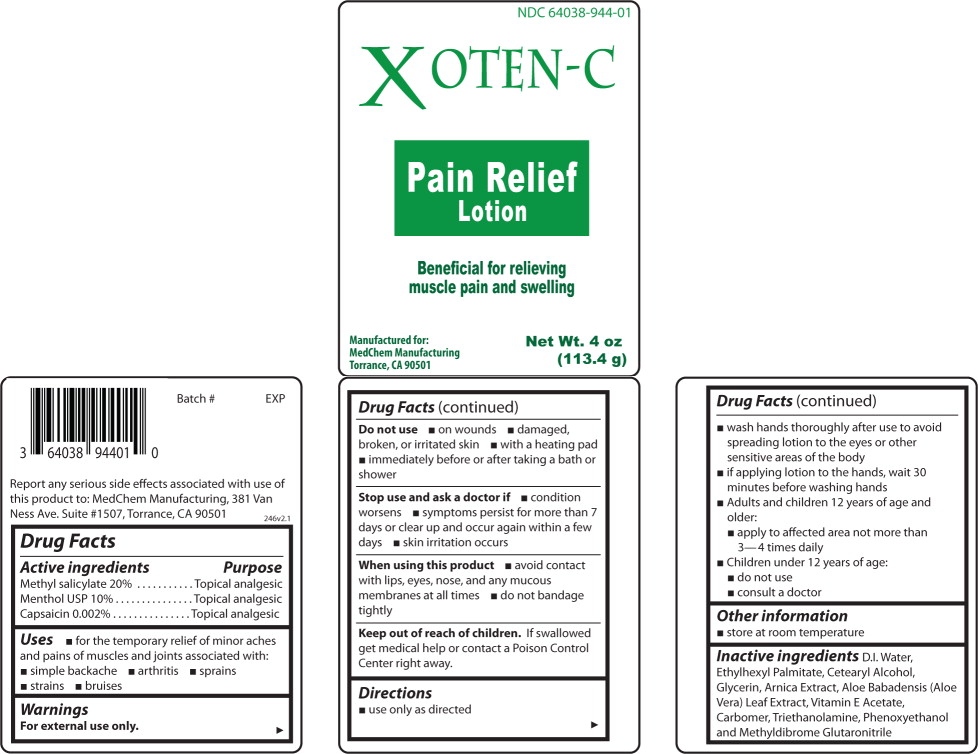 DRUG LABEL: XOTEN-C
NDC: 64038-944 | Form: LOTION
Manufacturer: Living Well Pharmacy Inc.
Category: otc | Type: HUMAN OTC DRUG LABEL
Date: 20110726

ACTIVE INGREDIENTS: Methyl salicylate 20 g/100 g; Menthol 10 g/100 g; Capsaicin 0.002 g/100 g
INACTIVE INGREDIENTS: Water; Ethylhexyl Palmitate; CETOSTEARYL ALCOHOL; Glycerin; ARNICA MONTANA; Aloe Vera Leaf; ALPHA-TOCOPHEROL ACETATE; TROLAMINE; Phenoxyethanol; METHYLDIBROMO GLUTARONITRILE

Drug Facts

Active ingredients

Methyl salicylate 20%

Menthol USP 10%

Capsaicin 0.002%

Purpose

Topical analgesic

Use

For the temporary relief of minor aches and pains of muscles and joints associated with:

- simple backache
- arthritis
- sprains
- strains
- bruises

Warnings

For external use only.

Do not use

- on wounds
- damaged, broken, or irritated skin
- with a heating pad
- immediately before or after taking a bath or shower

Stop use and ask a doctor if

- condition worsens
- symptoms persist for more than 7 days or clear up and occur again within a few days
- skin irritation occurs

When using this product

- avoid contact with lips, eyes, nose and any mucous membranes at all times
- do not bandage tightly

Keep out of reach of children.

If swallowed get medical help or contact Poison Control Center right away.

Directions

- use only as directed
- Wash hands thoroughly after use to avoid spreading lotion to the eyes or other sensitive areas of the body
- if applying lotion to the hands, wait 30 minutes before washing hands
- Adults and children 12 years of age and older:
  - apply to affected area not more than 3-4 times daily
- Children under 12 years of age:
  - do not use
  - consult a doctor

Other information

- Store at room temperature

Inactive ingredients

D.I. Water, Ethylhexyl Palmitate, Cetearyl Alcohol, Glycerin, Arnica Extract, Aloe Babadensis (Aloe Vera) Leaf Extract, Vitamin E Acetate, Carbomer, Triethanolamine, Phenoxyethanol and Methyldibrome Glutaronitrile

Principal Display Panel – Bottle Label

64038-094401

XOTEN-C

Pain Relief
Lotion

Beneficial for relieving
muscle pain and swelling

Manufactured for: Net Wt. 4 oz
MedChem Manufacturing (113.4 g)
Torrance, CA 90501